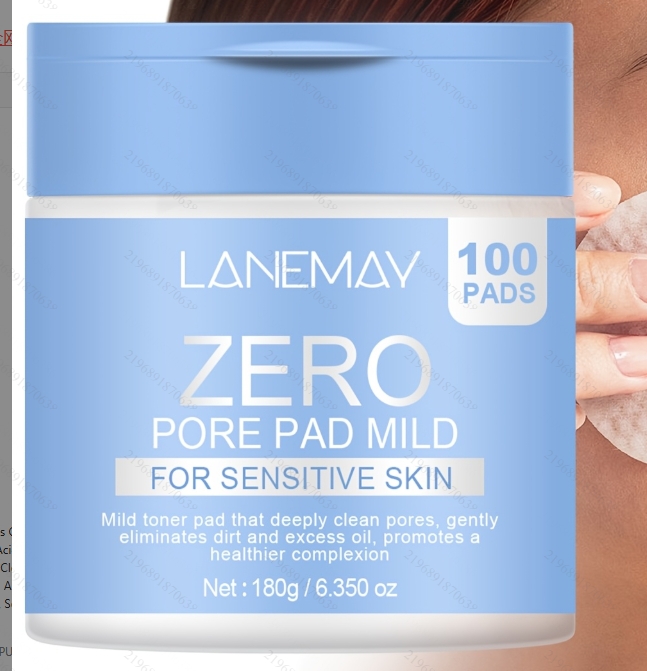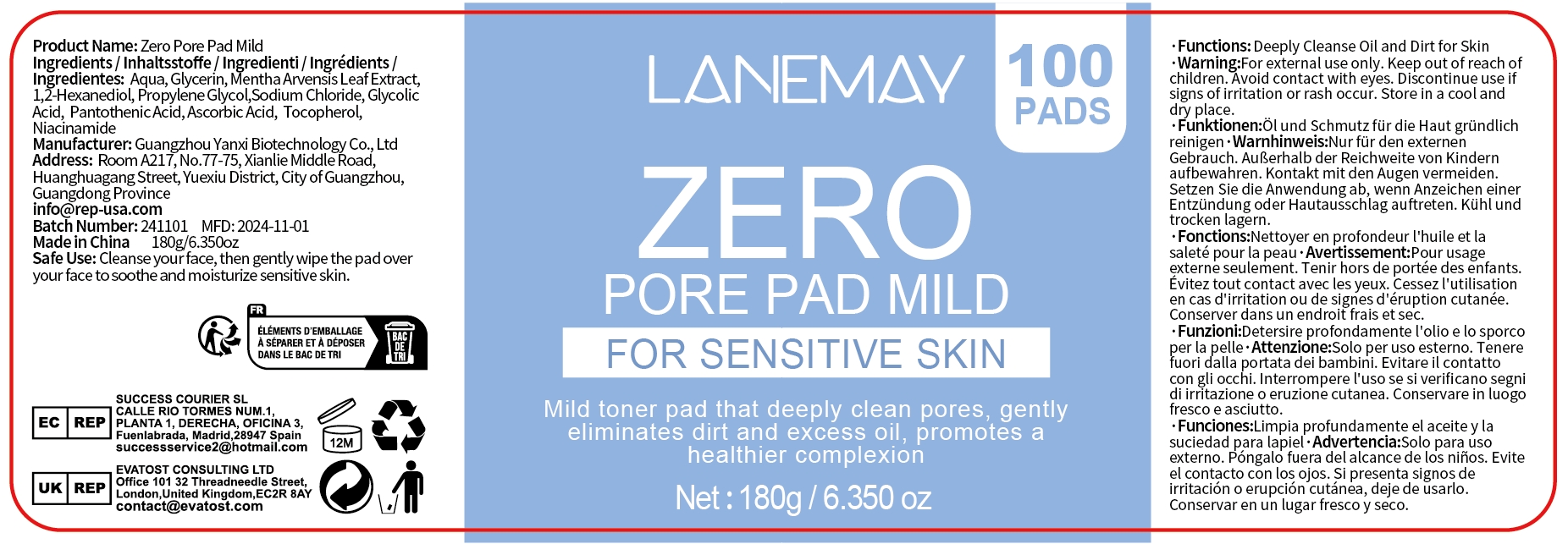 DRUG LABEL: Zero Pore Pad Mild
NDC: 84025-297 | Form: SWAB
Manufacturer: Guangzhou Yanxi Biotechnology Co., Ltd
Category: otc | Type: HUMAN OTC DRUG LABEL
Date: 20241225

ACTIVE INGREDIENTS: GLYCERIN 6 mg/180 g; NIACINAMIDE 4 mg/180 g
INACTIVE INGREDIENTS: WATER

DOSAGE AND ADMINISTRATION

Cleanse your face, then gently wipe the pad over your face to soothe and moisturize sensitive skin.

WARNINGS

Keep out of children

INACTIVE INGREDIENT

Aqua

INDICATIONS AND USAGE

For daily skin care

Keep out of children

PURPOSE

Deeply cleanse Oil and Dirt for Skin